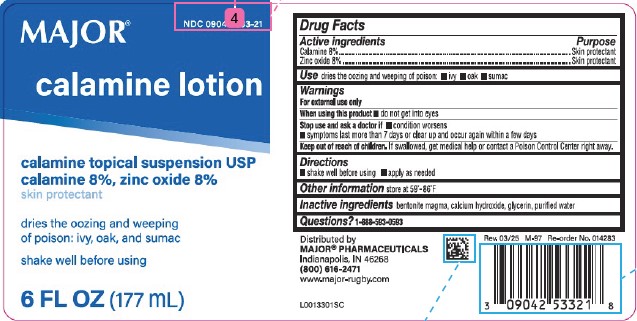 DRUG LABEL: Calamine
NDC: 0904-2533 | Form: LOTION
Manufacturer: Major Pharmaceuticals
Category: otc | Type: HUMAN OTC DRUG LABEL
Date: 20260204

ACTIVE INGREDIENTS: FERRIC OXIDE RED 80 mg/1 mL; ZINC OXIDE 80 mg/1 mL
INACTIVE INGREDIENTS: BENTONITE; CALCIUM HYDROXIDE; GLYCERIN; WATER

Major 063.001/063AA
Calamine Lotion

Active ingredients

Calamine 8%
Zinc oxide 8%

Purpose

Skin Protectant

Use

dries the oozing and weeping of poison:

- ivy
- oak
- sumac

Warnings

For external use only

When using this product

Do not get into eyes

Stop use and ask a doctor if

- condition worsens
- symptoms last more than 7 days or clear up and occur again within a few days

Keep out of reach of children.

If swallowed, get medical help or contact a Poison Control Center right away.

Directions

- shake well before using
- apply as needed

Other information

store at 59⁰ - 86⁰ F

Inactive ingredients

bentonite magma, calcium hydroxide, glycerin, purified water

Questions?

1-888-593-0593

Adverse reactions

Distributed By:

MAJOR®PHARMACEUTICALS

Indianapolis, IN 46268

(800) 616-2471

www.major-rugby.com

Rev. 03/25 M-97 Re-order No. 014283

principal display panel

NDC 0904-2533-21

MAJOR®

Calamine Lotion

Calamine Topical Suspension USP

Calamine 8%, Zinc Oxide 8%

Skin Protectant

dries the oozing and weeping of poison: ivy, oak, and sumac

Shake well before using

6 FL OZ (177 mL)